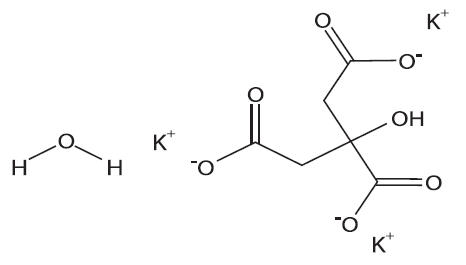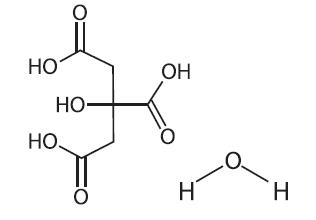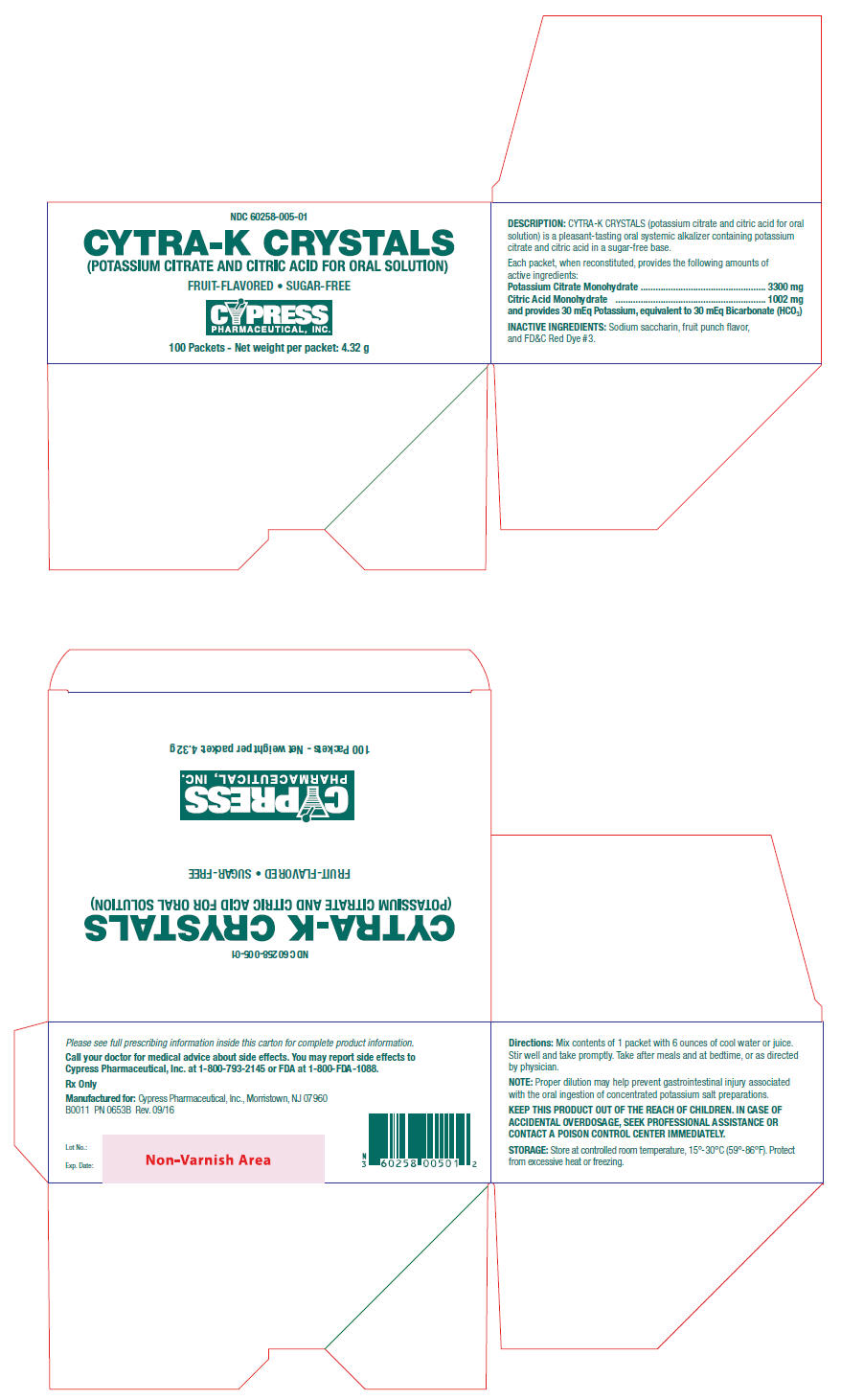 DRUG LABEL: Cytra-K Crystals
NDC: 60258-005 | Form: GRANULE, FOR SOLUTION
Manufacturer: Cypress Pharmaceutical, Inc.
Category: prescription | Type: HUMAN PRESCRIPTION DRUG LABEL
Date: 20160920

ACTIVE INGREDIENTS: Potassium Citrate 3.3 g/1 1; Citric Acid Monohydrate 1.002 g/1 1
INACTIVE INGREDIENTS: Saccharin Sodium Anhydrous 33 mg/1 1

CYTRA-K
CRYSTALS
(Potassium Citrate and
Citric Acid for Oral Solution)

Rx Only

NDC 60258-005-01

DESCRIPTION

CYTRA-K CRYSTALS (potassium citrate and citric acid for oral solution) is a pleasant-tasting oral systemic alkalizer containing potassium citrate and citric acid in a sugar-free base.

Each packet of CYTRA-K CRYSTALS, when reconstituted, provides the following amounts of active ingredients :

Potassium Citrate Monohydrate

3300 mg

Citric Acid Monohydrate

1002 mg

and provides 30 mEq potassium, equivalent to 30 mEq bicarbonate (HCO3).

INACTIVE INGREDIENTS

Sodium saccharin, fruit punch flavor, and FD&C Red Dye #3.

Potassium Citrate Monohydrate has the chemical name: 1,2,3-Propanetricarboxylic acid, 2-hydroxy-,tripotassium salt, monohydrate. Its chemical structure is as follows:

C6H5K3O7 ∙ H2O M.W. 324.41

Citric Acid Monohydrate has the chemical name: 1,2,3-Propanetricarboxylic acid, 2-hydroxy-, monohydrate. Its chemical structure is as follows:

C6H8O7 ∙ H2O M.W. 210.14

CLINICAL PHARMACOLOGY

Potassium citrate is absorbed and metabolized to potassium bicarbonate, thus acting as a systemic alkalizer. The effects are essentially those of chlorides before absorption and those of bicarbonates subsequently. Oxidation is virtually complete so that less than 5% of the potassium citrate is excreted in the urine unchanged.

INDICATIONS AND USAGE

CYTRA-K CRYSTALS is an effective alkalinizing agent useful in those conditions where long-term maintenance of an alkaline urine is desirable, such as in patients with uric acid and cystine calculi of the urinary tract, especially when the administration of sodium salts is undesirable or contraindicated. In addition, it is a valuable adjuvant when administered with uricosuric agents in gout therapy, since urates tend to crystallize out of an acid urine. It is also effective in correcting the acidosis of certain renal tubular disorders where the administration of potassium citrate may be preferable. CYTRA-K CRYSTALS is highly concentrated, and when administered after meals and before bedtime, allows one to maintain an alkaline urinary pH around the clock, usually without the necessity of a 2 A.M. dose. CYTRA-K CRYSTALS alkalinizes the urine without producing a systemic alkalosis in recommended dosage. It is highly palatable, pleasant tasting, and tolerable, even when administered for long periods. Potassium citrate does not neutralize the gastric juice or disturb digestion.

CONTRAINDICATIONS

Severe renal impairment with oliguria or azotemia, untreated Addison's disease, adynamia episodica hereditaria, acute dehydration, heat cramps, anuria, severe myocardial damage, and hyperkalemia from any cause. Known hypersensitivity to any ingredients in this product.

WARNINGS AND PRECAUTIONS

There have been several reports, published and unpublished, concerning nonspecific small-bowel lesions consisting of stenosis, with or without ulceration, associated with the administration of enteric-coated thiazides with potassium salts. These lesions may occur with enteric-coated potassium tablets alone or when they are used with nonenteric-coated thiazides, or certain other oral diuretics. These small-bowel lesions have caused obstruction, hemorrhage, and perforation. Surgery was frequently required and deaths have occurred. Based on a large survey of physicians and hospitals, both United States and foreign, the incidence of these lesions is low, and a causal relationship in man has not been definitely established. Available information tends to implicate enteric-coated potassium salts, although lesions of this type also occur spontaneously. Therefore, coated potassium-containing formulations should be administered only when indicated, and should be discontinued immediately if abdominal pain, distention, nausea, vomiting, or gastrointestinal bleeding occur. Large doses may cause hyperkalemia and alkalosis, especially in the presence of renal disease. Concurrent administration of potassium-containing medication, potassium-sparing diuretics, angiotensin-converting enzyme (ACE) inhibitors, or cardiac glycosides may lead to toxicity. Do not exceed recommended dosage. Discontinue use if adverse reactions occur.

Should be used with caution by patients with low urinary output unless under the supervision of a physician. As with all liquids containing a high concentration of potassium, patients should be directed to dilute adequately with water to minimize the possibility of gastrointestinal injury associated with the oral ingestion of concentrated potassium salt preparations; and preferably, to take each dose after meals to avoid saline laxative effect.

ADVERSE REACTIONS

CYTRA-K CRYSTALS is generally well tolerated without any unpleasant side effects when given in recommended doses to patients with normal renal function and urinary output. However, as with any alkalinizing agent, caution must be used in certain patients with abnormal renal mechanisms to avoid development of hyperkalemia or alkalosis. Potassium intoxication causes listlessness, weakness, mental confusion, tingling of extremities, and other symptoms associated with a high concentration of potassium in the serum. Periodic determinations of serum electrolytes should be carried out in those patients with renal disease in order to avoid these complications. Hyperkalemia may exhibit the following electrocardiographic abnormalities: Disappearance of the P wave, widening and slurring of QRS complex, changes of the S-T segment, tall peaked T waves, etc.

OVERDOSAGE

The administration of oral potassium salts to persons with normal excretory mechanisms for potassium rarely causes serious hyperkalemia. However, if excretory mechanisms are impaired, hyperkalemia can result (see Contraindications and Warnings). Hyperkalemia, when detected, must be treated immediately because lethal levels can be reached in a few hours.

Treatment

Should hyperkalemia occur, treatment measures include the following:

(1) Elimination of foods or medications containing potassium. (2) The intravenous administration of 300 to 500 mL/hr of dextrose solution (10 to 25%), containing 10 units of insulin /20 gm dextrose. (3) The use of exchange resins, hemodialysis, or peritoneal dialysis. In treating hyperkalemia, it should be recalled that in patients who have been stabilized on digitalis, too rapid a lowering of the plasma potassium concentration can produce digitalis toxicity.

DOSAGE AND ADMINISTRATION

CYTRA-K CRYSTALS should be taken mixed in cool water or juice according to directions, followed by additional water or juice, if desired. Proper dilution may help prevent gastroin-testinal injury associated with the oral ingestion of concentrated potassium salt preparations.

Usual Adult Dose

CYTRA-K CRYSTALS - Contents of 1 packet reconstituted with at least 6 ounces of cool water or juice, after meals and at bedtime, or as directed by physician.

Usual Pediatric Dose

CYTRA-K CRYSTALS is not recommended for pediatric use.

Usual Dosage Range

Contents of 1 packet CYTRA-K CRYSTALS, reconstituted as directed and taken four times a day, will usually maintain a urinary pH of 6.5-7.4. To check urinary pH, HYDRION Paper (pH 6.0-8.0) or NITRAZINE Paper (pH 4.5-7.5) are available and easy to use.

HOW SUPPLIED

CYTRA-K CRYSTALS - 100 Packets/box (NDC 60258-005-01).

STORAGE

Store at controlled room temperature, 15°-30°C (59°-86°F). Protect from excessive heat or freezing.

KEEP THIS PRODUCT OUT OF THE REACH OF CHILDREN. IN CASE OF ACCIDENTAL OVERDOSAGE, SEEK PROFESSIONAL ASSISTANCE OR CONTACT A POISON CONTROL CENTER IMMEDIATELY.

Call your doctor for medical advice about side effects. You may report side effects to Cypress Pharmaceutical, Inc. at 1-800-793-2145 or FDA at 1-800-FDA-1088.

Rx Only

Manufactured for: Cypress Pharmaceutical, Inc., Morristown, NJ 07960

I185
PN 0654C
Rev. 09/16

PRINCIPAL DISPLAY PANEL - 4.32 g Packet Box

NDC 60258-005-01

CYTRA-K CRYSTALS
(POTASSIUM CITRATE AND CITRIC ACID FOR ORAL SOLUTION)

FRUIT-FLAVORED • SUGAR-FREE

CYPRESS
PHARMACEUTICAL, INC.

100 Packets - Net weight per packet: 4.32 g